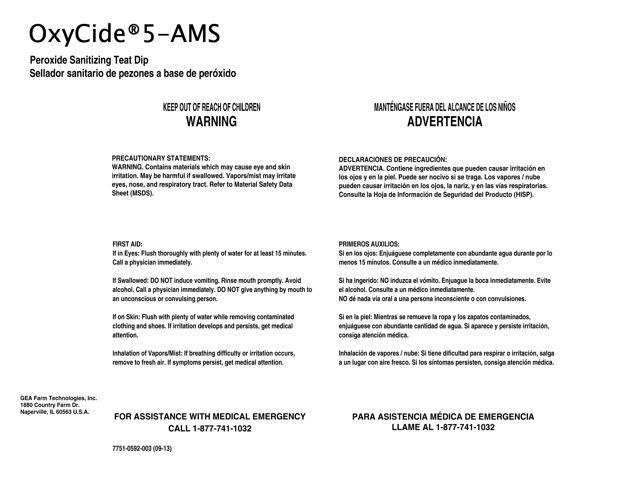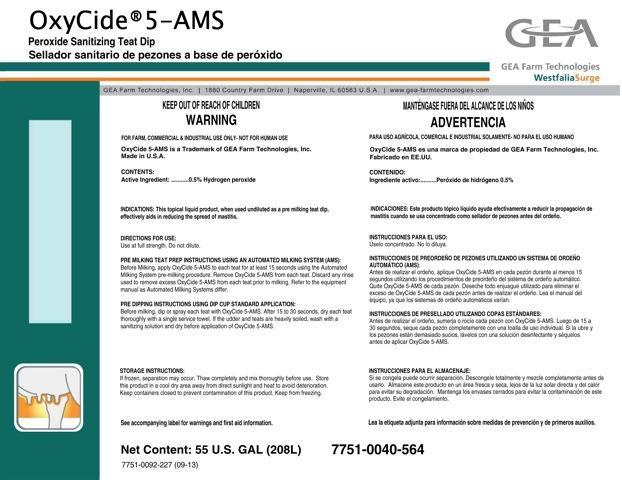 DRUG LABEL: OxyCide 5-AMS Peroxide Sanitizing Teat Dip
NDC: 51070-8009 | Form: LIQUID
Manufacturer: GEA Farm Technologies, Inc.
Category: animal | Type: OTC ANIMAL DRUG LABEL
Date: 20130911

ACTIVE INGREDIENTS: HYDROGEN PEROXIDE 0.5 L/100 L

OxyCide 5-AMS Peroxide Sanitizing Teat Dip

OxyCide 5-AMS GEA Farm Technologies WestfaliaSurge

Peroxide Sanitizing Teat Dip

GEA Farm Technologies, Inc. 1800 Country Farm Drive Naperville, IL 60563 U.S.A. www.gea-farmtechnologies.com

KEEP OUT OF REACH OF CHILDREN

WARNING

FOR FARM, COMMERCIAL AND INDUSTRIAL USE ONLY - NOT FOR HUMAN USE

ACTIVE INGREDIENT

CONTENTS:

Active Ingredient: ....... 0.5% Hydrogen peroxide

INDICATIONS AND USAGE

INDICATIONS:This topical liquid product, when used undiluted as a pre milking teat dip, effectively aids in reducing the spread of mastitis.

DOSAGE AND ADMINISTRATION

DIRECTIONS FOR USE:

Use at full strength. Do not dilute.

PRE MILKING TEAT PREP INSTRUCTIONS USING AN AUTOMATED MILKING SYSTEM (AMS):

Before Milking, apply OxyCide 5-AMS to each teat for at least 15 seconds using the Automated Milking System pre-milking procedure. Remove OxyCide 5-AMS from each teat. Discard any rinse used to remove excess OxyCide 5-AMS from each teat prior to milking. Refer to the equipment manual as Automated Milking Systems differ.

PRE DIPPING INSTRUCTIONS USING DIP CUP STANDARD APPLICATION:

Before milking, dip or spray each teat with OxyCide 5-AMS. After 15 to 30 seconds, dry each teat thoroughly with a single service towel. If the udder and teats are heavily soiled, wash with a sanitizing solution and dry before application of OxyCide 5-AMS.

STORAGE INSTRUCTIONS:

If frozen, separation may occur. Thaw completely and mix thoroughly before use. Store this product in a cool dry area away from direct sunlight and heat to avoid deterioration. Keep containers closed to prevent contamination of this product. Keep from freezing.

See accompanying label for warnings and first aid information.

Net Content: 55 U.S. Gal (208L)

7751-0092-227 (09-13)

GENERAL PRECAUTIONS

PRECAUTIONARY STATEMENTS:

WARNING: Contains material which may cause eye and skin irritation. May be harmful if swallowed. Vapors/mist may irritate eyes, nose, and respiratory tract. Refer to Material Safety Data Sheet (MSDS).

WARNINGS AND PRECAUTIONS

FIRST AID:

If in Eyes: Flush thoroughly with plenty of water for at least 15 minutes. Call a physician immediately.

If swallowed: DO NOT induce vomiting. Rinse mouth promptly. Avoid alcohol. Call a physician immediately. DO NOT give anything by mouth to an unconscious or convulsing person.

If on Skin: Flush with plenty of water while removing contaminated clothing and shoes. If irritation develops and persists, get medical attention.

Inhalation of Vapors/Mist: If breathing difficulty or irritation occurs, remove to fresh air. If symptoms persist, get medical attention.

FOR ASSISTANCE WITH MEDICAL EMERGENCY

CALL 1-877-741-1032